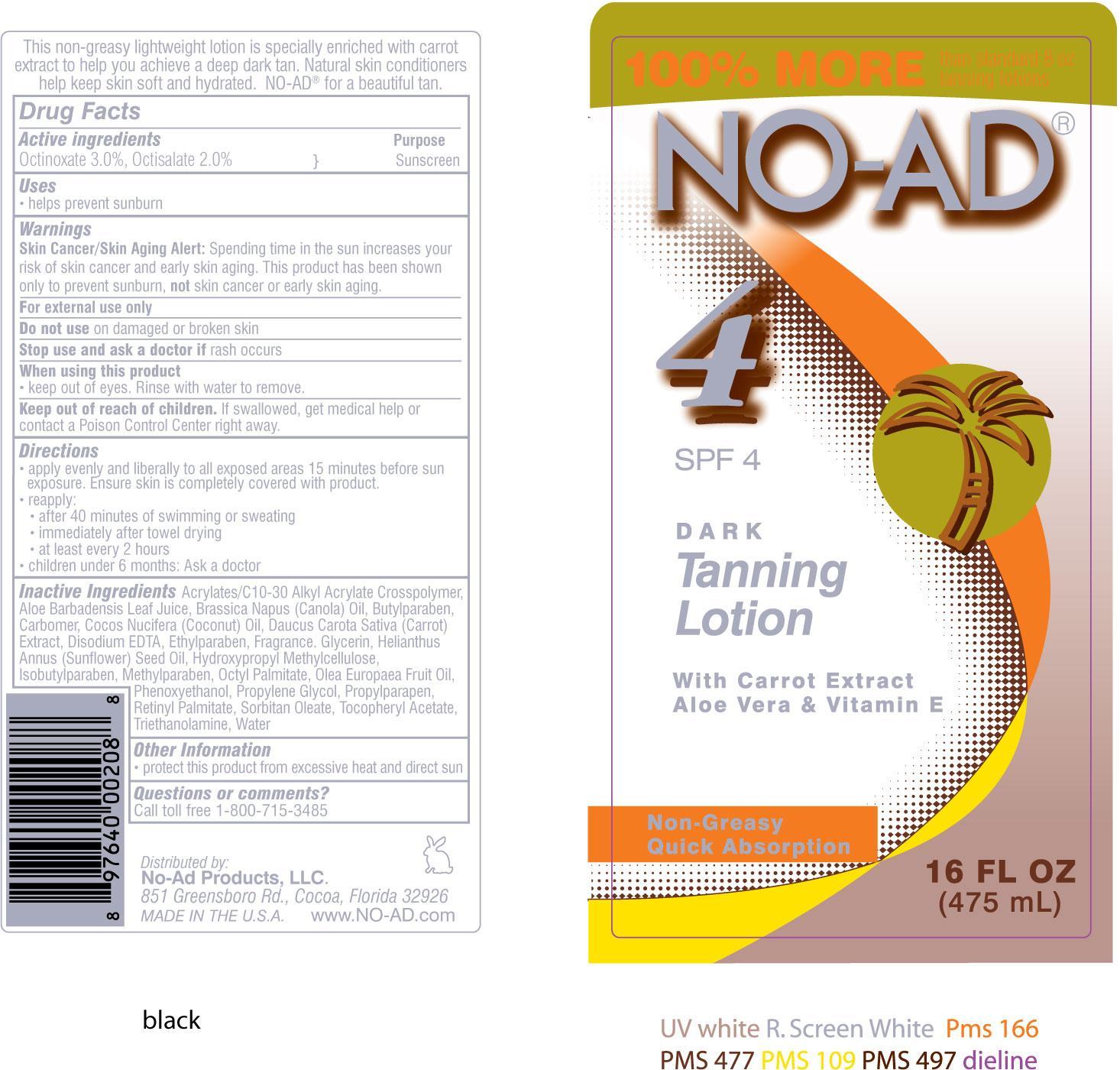 DRUG LABEL: NO-AD Dark Tanning SPF 4
NDC: 62802-208 | Form: LOTION
Manufacturer: Sun & Skin Care Research, LLC
Category: otc | Type: HUMAN OTC DRUG LABEL
Date: 20140304

ACTIVE INGREDIENTS: OCTINOXATE 3 g/100 g; OCTISALATE 2 g/100 g
INACTIVE INGREDIENTS: ALOE VERA LEAF; CANOLA OIL; BUTYLPARABEN; CARBOMER HOMOPOLYMER TYPE C; COCONUT OIL; CARROT SEED OIL; EDETATE DISODIUM; VITAMIN A PALMITATE; ETHYLPARABEN; GLYCERIN; SUNFLOWER OIL; HYPROMELLOSE 2910 (4000 MPA.S); ISOBUTYLPARABEN; METHYLPARABEN; ETHYLHEXYL PALMITATE; OLIVE OIL; PHENOXYETHANOL; PROPYLENE GLYCOL; .ALPHA.-TOCOPHEROL ACETATE; SORBITAN MONOOLEATE; TROLAMINE; WATER

DRUG FACTS

Active Ingredients

Octinoxate 3.0%
Octisalate 2.0%

Purpose

Sunscreen

Uses

- Helps prevent sunburn

Warnings

Skin Cancer / Skin Aging Alert: Spending time in the sun increases your risk of skin cancer and early skin aging. This product has been shown only to prevent sunburn, not skin cancer or early skin aging.

For external use only. Do not use on damaged or broken skin. Stop use and ask a doctor if rash occurs. When using this product keep out of eyes. Rinse with water to remove. Keep out of the reach of children. If swallowed, get medical help or call a poison control center right away.

Directions

- apply evenly and liberally to all exposed areas 15 minutes before sun exposure. Ensure skin is completely covered with product.
- reapply after 40 minutes of swimming or sweating, immediately after towel drying and at least every 2 hours
- children under 6 months: Ask a doctor

Other Information

- protect this product from excessive heat and direct sun
- for use on skin only
- avoid contact with fabric